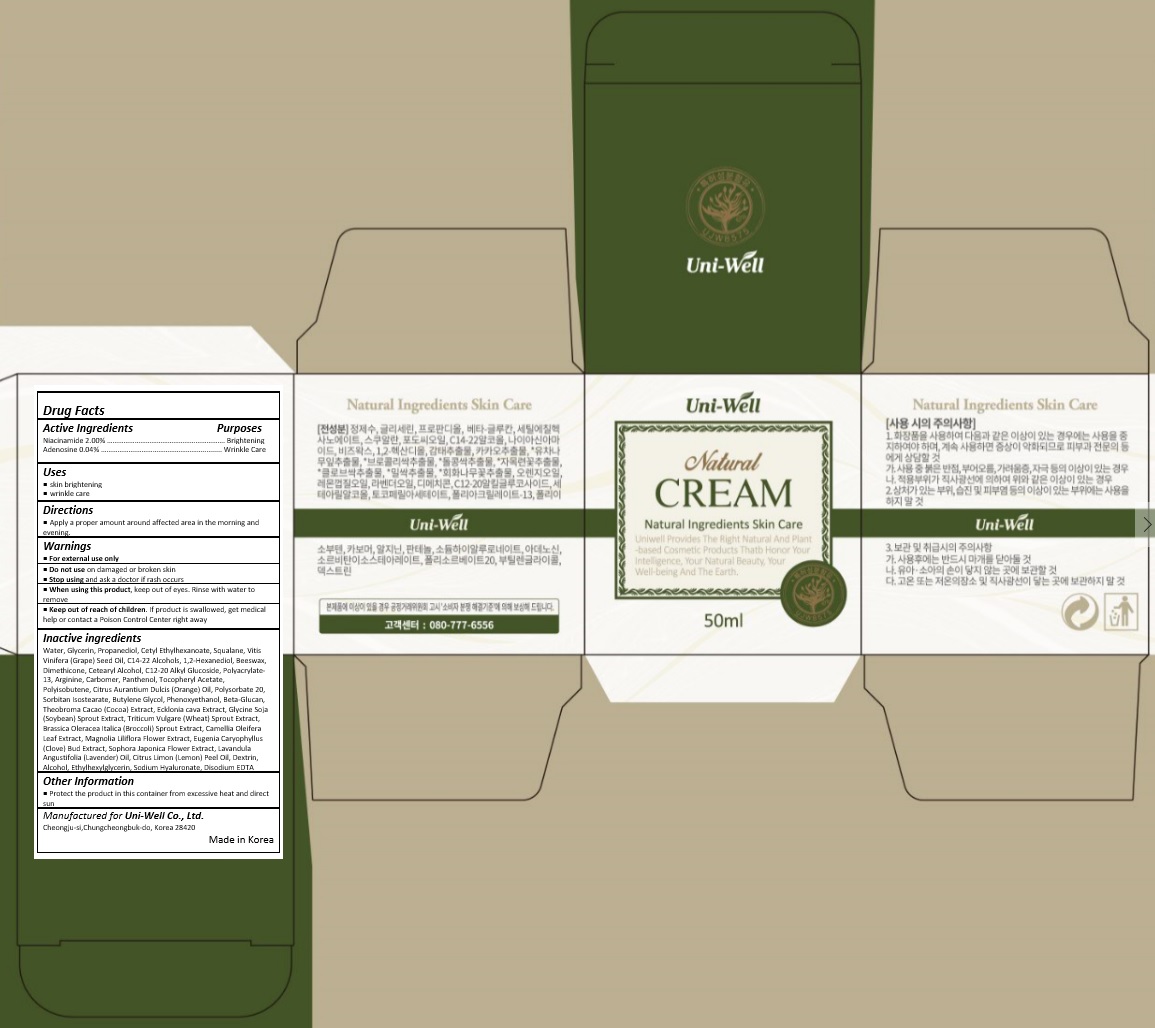 DRUG LABEL: UNIWELL NATURAL
NDC: 71502-003 | Form: CREAM
Manufacturer: uniwell LTD
Category: otc | Type: HUMAN OTC DRUG LABEL
Date: 20170614

ACTIVE INGREDIENTS: NIACINAMIDE 1 mg/50 mL; ADENOSINE 0.02 mg/50 mL
INACTIVE INGREDIENTS: ARGININE; PANTHENOL; .ALPHA.-TOCOPHEROL ACETATE; WATER; GLYCERIN; PROPANEDIOL; CETYL ETHYLHEXANOATE; SQUALANE; GRAPE SEED OIL; C14-22 ALCOHOLS; 1,2-HEXANEDIOL; YELLOW WAX; DIMETHICONE; CETOSTEARYL ALCOHOL; C12-20 ALKYL GLUCOSIDE; POLYACRYLAMIDE (1500 MW); POLYISOBUTYLENE (1000 MW); ORANGE OIL; POLYSORBATE 20; SORBITAN ISOSTEARATE; BUTYLENE GLYCOL; PHENOXYETHANOL; COCOA; ECKLONIA CAVA; SOYBEAN; WHEAT SPROUT; BROCCOLI SPROUT; CAMELLIA OLEIFERA LEAF; MAGNOLIA LILIIFLORA FLOWER; CLOVE; STYPHNOLOBIUM JAPONICUM FLOWER; LAVENDER OIL; LEMON OIL; ALCOHOL; ETHYLHEXYLGLYCERIN; HYALURONATE SODIUM; EDETATE DISODIUM ANHYDROUS

Drug Facts

ACTIVE INGREDIENT

NIACINAMIDE 2.00%

ADENOSINE 0.04%

PURPOSE

Brighting and Wrinkle Care

INDICATIONS AND USAGE

skin brightening
wrinkle care

DOSAGE AND ADMINISTRATION

Apply a proper amount around affected area in the morning and evening.

WARNINGS

For external use only.
Do not use on damaged or broken skin.
When using this product, keep out of eyes. Rinse with water to remove.
Stop using and ask a doctor if rash occurs.

KEEP OUT OF REACH OF CHILDREN

Keep out of reach of the children. If product is swallowed, get medical help or contact a poison control center right away.

INACTIVE INGREDIENT

Water, Glycerin, Propanediol, Cetyl Ethylhexanoate, Squalane, Vitis Vinifera (Grape) Seed Oil, C14-22 Alcohols, 1,2-Hexanediol, Beeswax, Dimethicone, Cetearyl Alcohol, C12-20 Alkyl Glucoside, Polyacrylate-13, Arginine, Carbomer, Panthenol, Tocopheryl Acetate, Polyisobutene, Citrus Aurantium Dulcis (Orange) Oil, Polysorbate 20, Sorbitan Isostearate, Butylene Glycol, Phenoxyethanol, Beta-Glucan, Theobroma Cacao (Cocoa) Extract, Ecklonia cava Extract, Glycine Soja (Soybean) Sprout Extract, Triticum Vulgare (Wheat) Sprout Extract, Brassica Oleracea Italica (Broccoli) Sprout Extract, Camellia Oleifera Leaf Extract, Magnolia Liliflora Flower Extract, Eugenia Caryophyllus (Clove) Bud Extract, Sophora Japonica Flower Extract, Lavandula Angustifolia (Lavender) Oil, Citrus Limon (Lemon) Peel Oil, Dextrin, Alcohol, Ethylhexylglycerin, Sodium Hyaluronate, Disodium EDTA